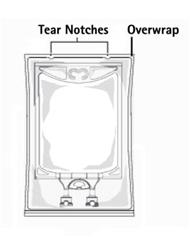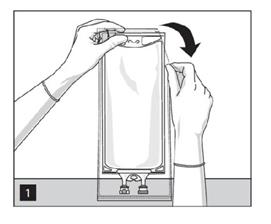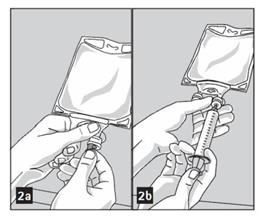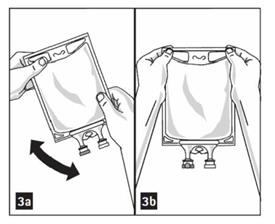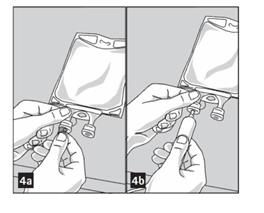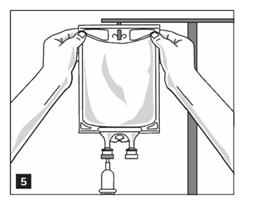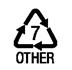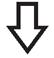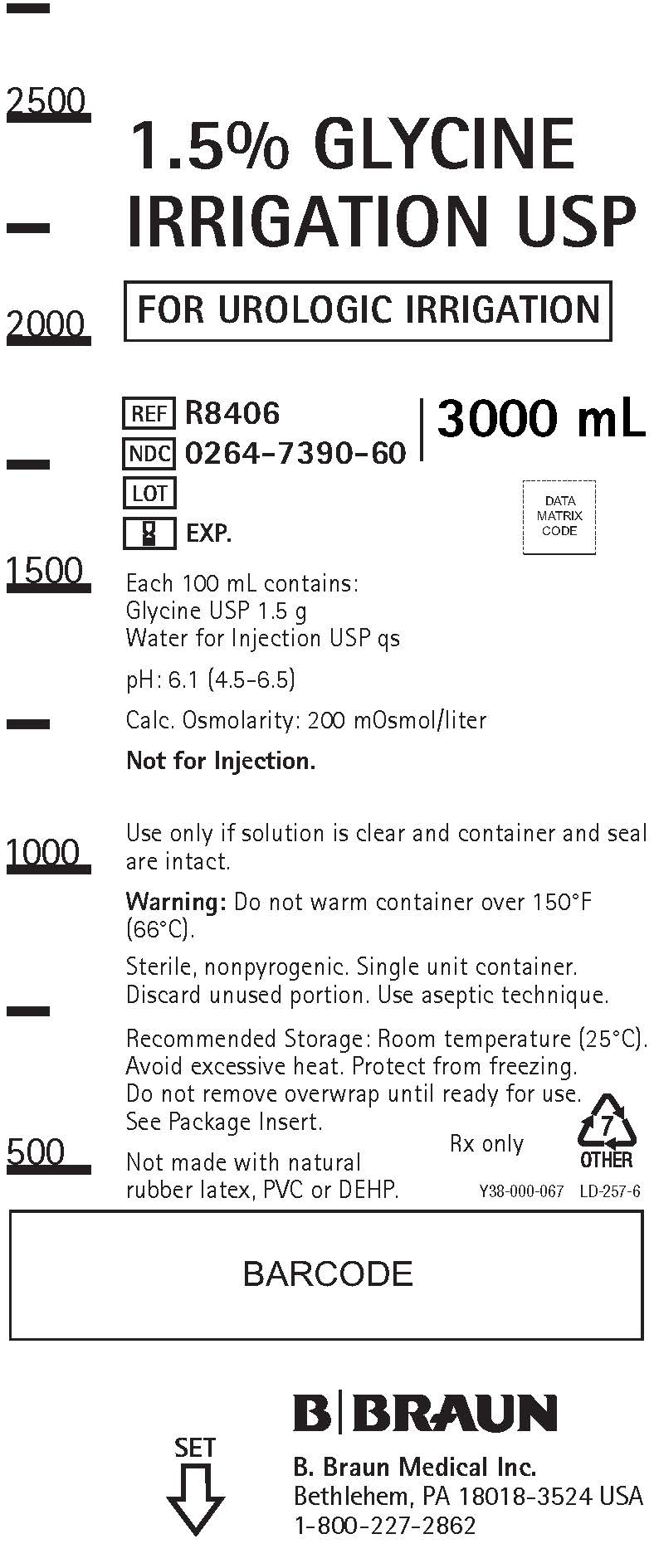 DRUG LABEL: Glycine
NDC: 0264-7390 | Form: IRRIGANT
Manufacturer: B. Braun Medical Inc.
Category: prescription | Type: HUMAN PRESCRIPTION DRUG LABEL
Date: 20210401

ACTIVE INGREDIENTS: GLYCINE 1.5 g/100 mL
INACTIVE INGREDIENTS: WATER

1.5% Glycine Irrigation USP

DESCRIPTION

Each 100 mL contains:

Glycine USP ..................................................................................... 1.5 g
Water for Injection USP ................................................................... qs

pH: 6.1 (4.5-6.5)
Calculated Osmolarity: 200 mOsmol/liter

The formula of the active ingredient is:

Ingredient | Molecular Formula | Molecular Weight
Glycine USP | NH2CH2COOH | 75.07

1.5% Glycine Irrigation USP is a sterile, nonpyrogenic aqueous solution suitable for urologic irrigation. This solution is slightly hypotonic.

The plastic container is made from a multilayered film specifically developed for parenteral drugs. It contains no plasticizers and exhibits virtually no leachables. The solution contact layer is a rubberized copolymer of ethylene and propylene. The container is nontoxic and biologically inert. The container-solution unit is a closed system and is not dependent upon entry of external air during administration. The container is overwrapped to provide protection from the physical environment and to provide an additional moisture barrier when necessary.

Not made with natural rubber latex, PVC or DEHP.

CLINICAL PHARMACOLOGY

1.5% Glycine Irrigation USP is nontoxic and nonhemolytic with a refractive index close to that of water. These properties make it useful as a urologic irrigating fluid, particularly during transurethral surgical procedures where the irrigant may be absorbed through cut venous sinuses.

Systemically absorbed glycine is primarily metabolized by transamination to serine, and by deamination to ammonia which is normally removed by its conversion to urea. A portion of the absorbed glycine is excreted by the kidneys.

INDICATIONS AND USAGE

1.5% Glycine Irrigation USP is indicated as an irrigant during transurethral prostatic or bladder surgery.

CONTRAINDICATIONS

1.5% Glycine Irrigation USP is not for injection. It is contraindicated in patients with anuria.

WARNINGS

Solutions for urologic irrigation must be used with caution in patients with severe cardiopulmonary or renal dysfunction.

The amount of fluid absorbed during a transurethral resection is a function of the volume and hydrostatic pressure of the irrigant used, the number and size of venous sinuses opened, and the duration of the procedure. Since irrigating fluids used during transurethral prostatectomy have been demonstrated to enter the systemic circulation in relatively large volumes, any irrigation solution must be regarded as a systemic drug.

Absorption of large amounts of fluids containing glycine and the resultant osmotic diuresis may significantly affect cardiopulmonary and renal dynamics. Absorption of large amounts of irrigating solution can also result in pronounced hyponatremia and water intoxication.

After opening container, the contents should be used promptly to minimize the possibility of bacterial growth or pyrogen formation.

Discard unused portion of irrigating solution since it contains no preservative.

PRECAUTIONS

Cardiovascular status, especially in patients with cardiac disease, should be carefully determined before and during transurethral resection of the prostate when using 1.5% Glycine Irrigation USP as an irrigant. The fluid absorbed into the systemic circulation via severed prostatic veins may produce significant extracellular fluid expansion and lead to fulminating congestive heart failure.

Shift of sodium-free intracellular fluid into the extracellular compartment following systemic absorption of 1.5% Glycine Irrigation USP may lower serum sodium concentration and aggravate pre-existing hyponatremia.

Excessive loss of water and electrolytes may lead to serious imbalances. Sustained diuresis from transurethral irrigation with 1.5% Glycine Irrigation USP may obscure and intensify inadequate hydration or hypovolemia.

Care should be exercised if impaired liver function is known or suspected. Under such conditions, ammonia resulting from the metabolism of glycine may accumulate in the blood.

Use only if solution is clear and container and seal are intact.

ADVERSE REACTIONS

Adverse reactions may include fluid and electrolyte disorders such as acidosis, electrolyte loss, marked diuresis, urinary retention, edema and dehydration; cardiovascular/pulmonary disorders such as pulmonary congestion, hypotension, tachycardia, angina-like pain and thrombophlebitis; other possible reactions include visual disturbances, convulsions, nausea, vomiting, diarrhea, vertigo and urticaria.

Literature includes reports on hyponatremia, hyperammonemia, transient blindness, coma (immediate or delayed), and digitalis toxicity in digitalized patients.

If an adverse reaction occurs, discontinue the irrigant and reevaluate the clinical status of the patient.

DOSAGE AND ADMINISTRATION

As required for irrigation.

1.5% Glycine Irrigation USP should be administered only by the appropriate transurethral urologic instrumentation.

It has been reported that absorption is significantly increased if the container is higher than 60 cm (24 inches) above the patient.

This drug product should be inspected visually for particulate matter and discoloration prior to administration, whenever solution and container permit.

HOW SUPPLIED

1.5% Glycine Irrigation USP is supplied sterile and nonpyrogenic in single-dose 3000 mL flexible irrigation containers packaged 4 per case.

NDC | REF | Size
0264-7390-60 | R8406 | 3000 mL

STORAGE AND HANDLING

Exposure of pharmaceutical products to heat should be minimized. Avoid excessive heat. Protect from freezing. It is recommended that the product be stored at room temperature (25°C); however, brief exposure up to 40°C does not adversely affect the product.

Do not warm container over 150°F (66°C).

Rx only

Revised: January 2019

Instructions for Preparation and Administration

For Irrigation Use Only.

Not for injection.

Not for use with pressurized irrigation systems.

Aseptic technique is required.

- Inspect irrigation bag: overwrap and primary bag.
- Do not use if overwrap has been damaged.
- Do not use unless solution is clear and closure is intact.

1. To open: Tear overwrap starting from the tear notches. (Figure 1)

2. Prepare medication port by removal of aluminum foil. (Figure 2a)

- Puncture resealable medication port by using 19 – 22 gauge needle and inject additive(s). (Figure 2b)

- Medication port must be swabbed with disinfection agent before re-puncturing.
- Mix solution and medication thoroughly. (Figure 3a)
- Check admixture visually for particulate matter. (Figure 3b)

3. Remove aluminum foil from outlet/set port at the bottom of container (Figure 4a) and attach administration set (Figure 4b): use non-vented infusion set or close air vent on a vented set. Refer to directions for use accompanying the administration set.

4. Hang bag on IV Pole. (Figure 5)

B. Braun Medical Inc.
Bethlehem, PA 18018-3524 USA
1-800-227-2862

Y36-002-992 LD-412-5

PRINCIPAL DISPLAY PANEL - 3000 mL

1.5% GLYCINE
IRRIGATION USP

FOR UROLOGIC IRRIGATION

REF R8406
NDC 0264-7390-60
LOT
EXP.

3000 mL

Each 100 mL contains:
Glycine USP 1.5 g
Water for Injection USP qs

pH: 6.1 (4.5-6.5)

Calc. Osmolarity: 200 mOsmol/liter

Not for Injection.

Use only if solution is clear and container and seal
are intact.

Warning: Do not warm container over 150°F
(66°C).

Sterile, nonpyrogenic. Single unit container.
Discard unused portion. Use aseptic technique.

Recommended Storage: Room temperature (25°C).
Avoid excessive heat. Protect from freezing.
Do not remove overwrap until ready for use.
See Package Insert.

Not made with natural
rubber latex, PVC or DEHP.

Rx only

Y38-000-067 LD-257-6

SET

B. Braun Medical Inc.
Bethlehem, PA 18018-3524 USA
1-800-227-2862

Y38-000-067